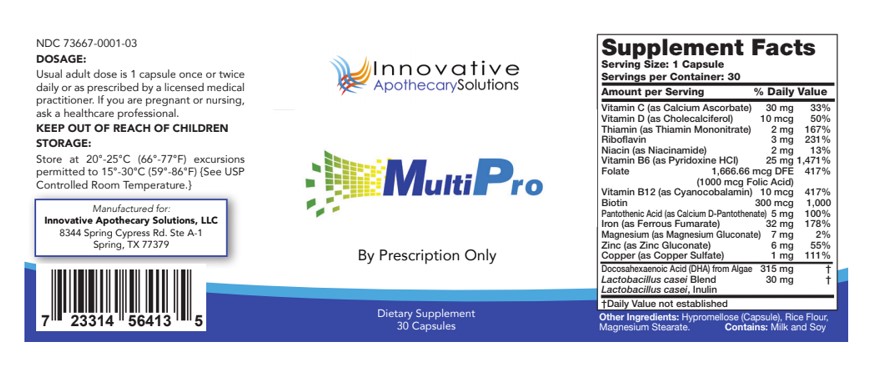 DRUG LABEL: Multi Pro
NDC: 73667-001 | Form: CAPSULE
Manufacturer: Innovative Apothecary Solutions
Category: other | Type: Dietary Supplement
Date: 20200605

ACTIVE INGREDIENTS: CALCIUM ASCORBATE 30 mg/1 1; THIAMINE MONONITRATE 2 mg/1 1; RIBOFLAVIN 3 mg/1 1; NIACINAMIDE 2 mg/1 1; CYANOCOBALAMIN 10 ug/1 1; PYRIDOXINE HYDROCHLORIDE 25 mg/1 1; FOLIC ACID 1 mg/1 1; ZINC GLUCONATE 6 mg/1 1; BIOTIN 300 ug/1 1; FERROUS FUMARATE 3 ug/1 1; MAGNESIUM GLUCONATE 7 mg/1 1; CALCIUM PANTOTHENATE 5 mg/1 1
INACTIVE INGREDIENTS: CHOLECALCIFEROL 10 ug/1 1; BASIC COPPER SULFATE 1 mg/1 1

MultiPro

Dosage

Adult Dose is 1 capsule once or twice daily or as prescribed by a licensed medical practitioner.

If Pregnant

If pregnant or nursing ask a healthcare professional.

Keep Out of Reach of Children

Storage

Store at 20°-25°C (66°-77°) excursions permitted to 15°-30°(59°-86°F).

Description

MultiPro is a dietary supplement intended for oral administration

Indication and Usage

For Prescription Only